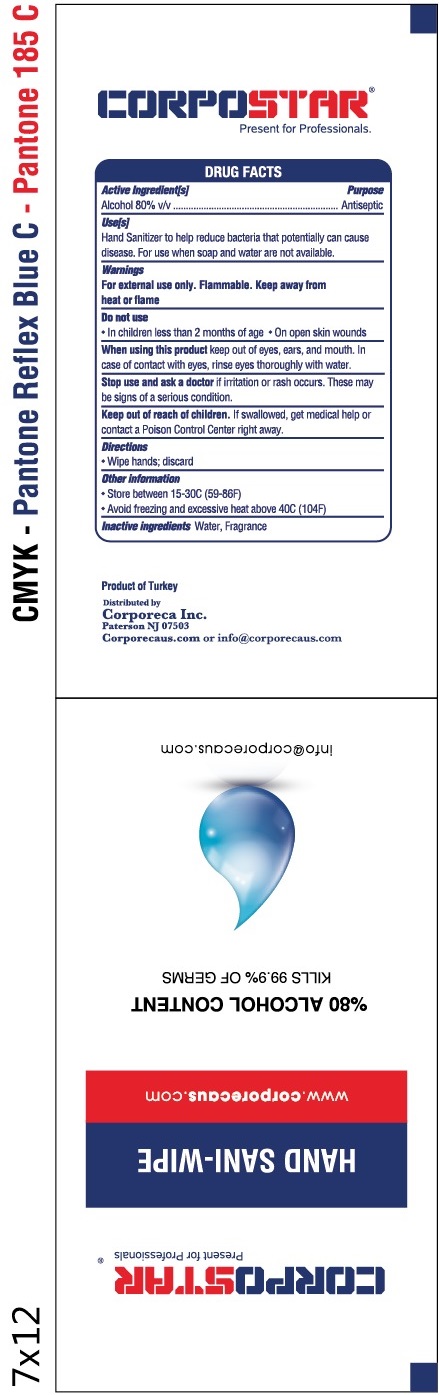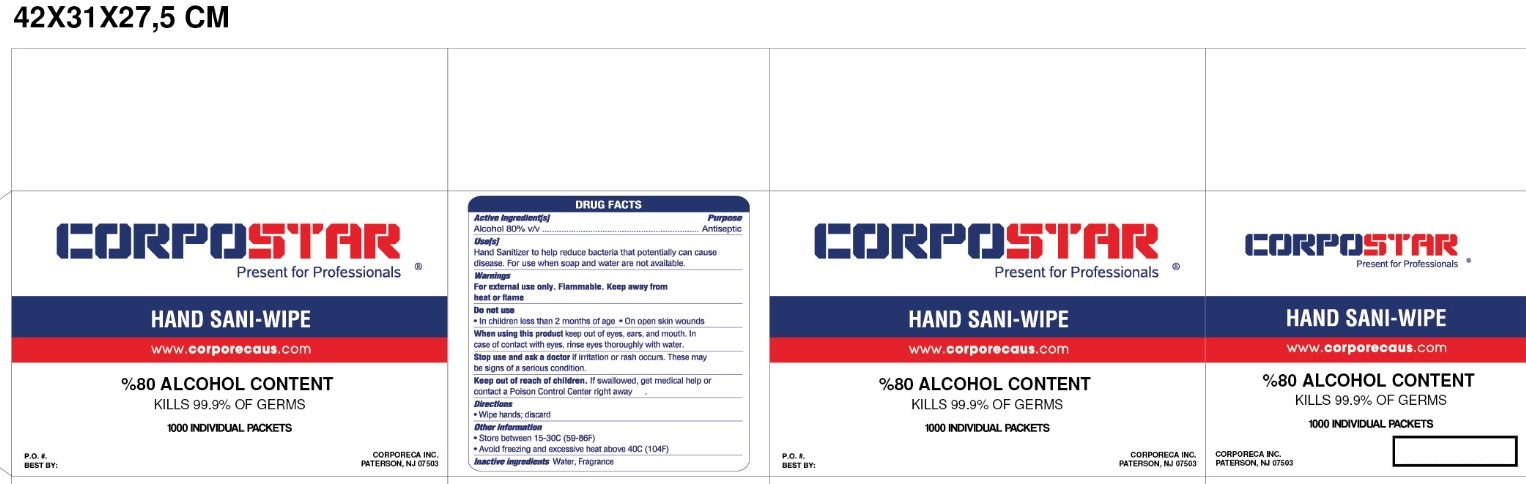 DRUG LABEL: Corpostar Hand Sani Wipe
NDC: 81099-001 | Form: CLOTH
Manufacturer: Corporeca Inc
Category: otc | Type: HUMAN OTC DRUG LABEL
Date: 20201120

ACTIVE INGREDIENTS: ALCOHOL 0.8 mL/1 mL
INACTIVE INGREDIENTS: WATER

Corpostar Hand Sani-Wipe

Active Ingredient[s]

Alcohol 80 % v/v

Purpose

Antiseptic

Use[s]

Hand Sanitizer to help reduce bacteria that potentially can cause disease. For use when soap and water are not available.

Warnings

For external use only. Flammable. Keep away from heat or flame

Do not use

- In children less than 2 months of age
- On open skin wounds

When using this product

keep out of eyes, ears, and mouth. In case of contact with eyes, rinse eyes thoroughly with water.

Stop use and ask a doctor

if irritation or rash occurs. These may be signs of a serious condition.

Keep out of reach of children.

If swallowed, get medical help or contact a Poison Control Center right away.

Directions

Wipe hands; discard

Other information

- Store between 15-30C (59-86F)
- Avoid freezing and excessive heat above 40C (104F)

Inactive ingredients

Water, Fragrance